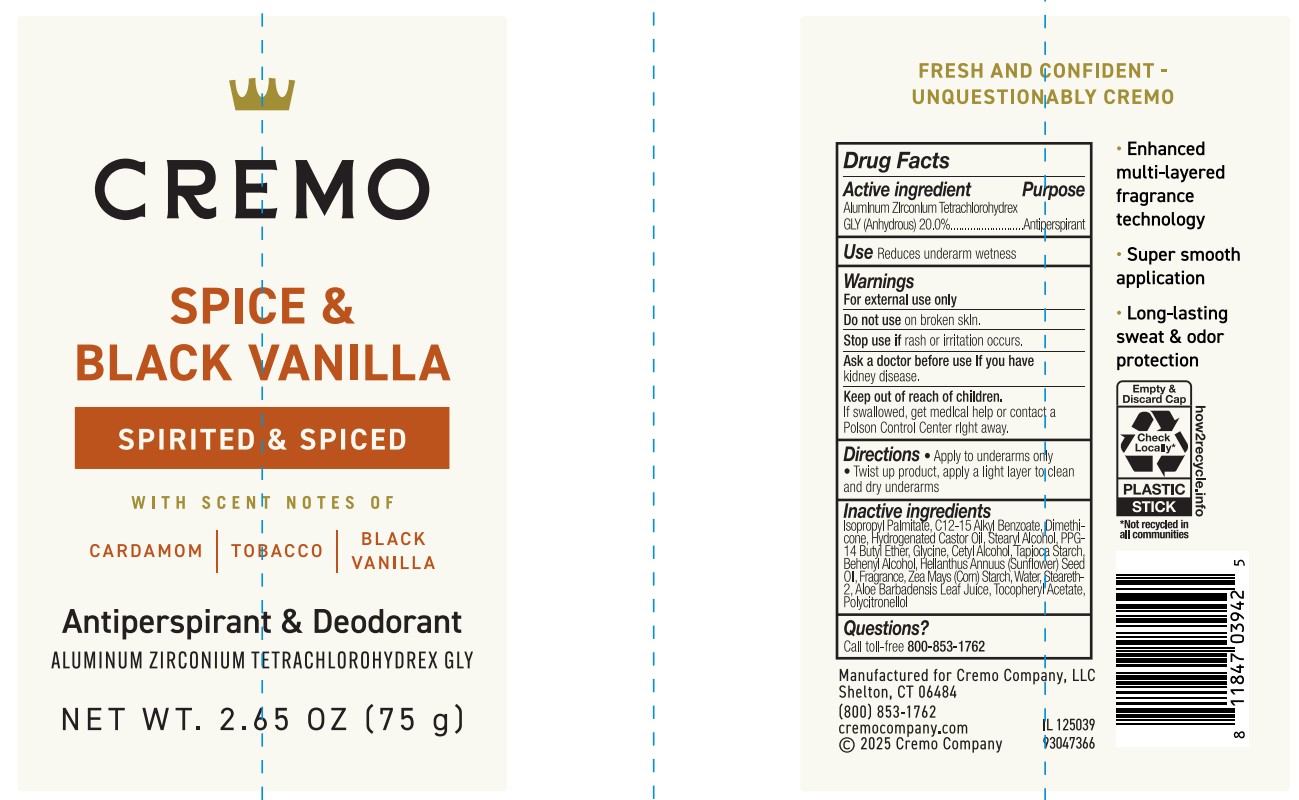 DRUG LABEL: Cremo Company
NDC: 71825-541 | Form: STICK
Manufacturer: Cremo Company
Category: otc | Type: HUMAN OTC DRUG LABEL
Date: 20260101

ACTIVE INGREDIENTS: ALUMINUM ZIRCONIUM TETRACHLOROHYDREX GLY 20 g/100 mL
INACTIVE INGREDIENTS: DIMETHICONE; STEARYL ALCOHOL; HELIANTHUS ANNUUS (SUNFLOWER) SEED OIL; C12-15 ALKYL BENZOATE; ZEA MAYS (CORN) STARCH; PPG-14 BUTYL ETHER; BEHENYL ALCOHOL; STEARETH-2; ISOPROPYL PALMITATE; HYDROGENATED CASTOR OIL; WATER; .ALPHA.-TOCOPHEROL ACETATE; CETYL ALCOHOL; ALOE BARBADENSIS LEAF JUICE; TAPIOCA STARCH; GLYCINE

Active Ingredient

Aluminum Zirconium Tetrachlorohydrex GLY (Anhydrous) (20.0%)

Purpose

Antiperspirant

Use

Reduces underarm wetness

Warnings

For external use only

Do not use

on broken skin.

Stop use if

skin rash or irritation occurs.

Ask a doctor before use if you have

kidney disease.

Keep out of reach of children.

If swallowed, get medical help or contact a Poison Control Center right away.

Directions

• Apply to underarms only. • Twist up product, apply a light layer to clean and dry underarms.

Inactive ingredients

Isopropyl Palmitate, C12-15 Alkyl Benzoate, Dimethicone, Hydrogenated Castor Oil, Stearyl Alcohol, PPG-14 Butyl Ether, Glycine, Cetyl Alcohol, Tapioca Starch, Behenyl Alcohol, Helianthus Annuus (Sunflower) Seed Oil, Zea Mays (Corn) Starch, Fragrance, Water, Steareth-2, Aloe Barbadensis Leaf Juice, Tocopheryl Acetate, Polycitronellol.

Questions

Call toll-free 800-853-1762

PACKAGE LABEL

Cremo
SPICE & BLACK VANILLA
SPIRITED & SPICED
WITH SCENT NOTES OF
CARDAMOM| TOBACCO| BLACK VANILLA
Antiperspirant & Deodorant
ALUMINUM ZIRCONIUM TETRACHLOROHYDREX GLY
NET WT. 2.65 OZ (75 g)